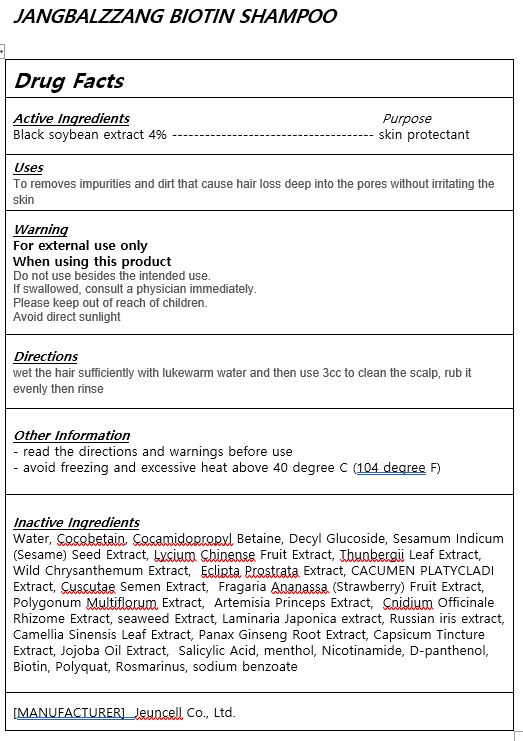 DRUG LABEL: JANGBALZZANG BIOTINshampoo
NDC: 54296-0004 | Form: SHAMPOO
Manufacturer: Jeuncell Co.,Ltd
Category: otc | Type: HUMAN OTC DRUG LABEL
Date: 20230922

ACTIVE INGREDIENTS: SOYBEAN OIL 4 g/100 mL
INACTIVE INGREDIENTS: WATER; JOJOBA OIL

ACTIVE INGREDIENT

black soybean extracts

INACTIVE INGREDIENT

Water, Cocobetain, Cocamidopropyl Betaine, Decyl Glucoside, Sesamum Indicum (Sesame) Seed Extract, Lycium Chinense Fruit Extract, Thunbergii Leaf Extract, Wild Chrysanthemum Extract, Eclipta Prostrata Extract, CACUMEN PLATYCLADI Extract, Cuscutae Semen Extract, Fragaria Ananassa (Strawberry) Fruit Extract, Polygonum Multiflorum Extract, Artemisia Princeps Extract, Cnidium Officinale Rhizome Extract, seaweed Extract, Laminaria Japonica extract, Russian iris extract, Camellia Sinensis Leaf Extract, Panax Ginseng Root Extract, Capsicum Tincture Extract, Jojoba Oil Extract, Salicylic Acid, menthol, Nicotinamide, D-panthenol, Biotin, Polyquat, Rosmarinus, sodium benzoate

PURPOSE

Weak acidic shampoo has a structure that protects our skin, so it does not damage the scalp and is good for scalp health.

WARNINGS

Do not use besides the intended use.
If swallowed, consult a physician immediately.
Please keep out of reach of children.
Avoid direct sunlight

Please keep out of reach of children.

Uses

to clean scalp and norishment

Directions

wet the hair sufficiently with lukewarm water and then use 3cc to clean the scalp, rub it evenly then rinse